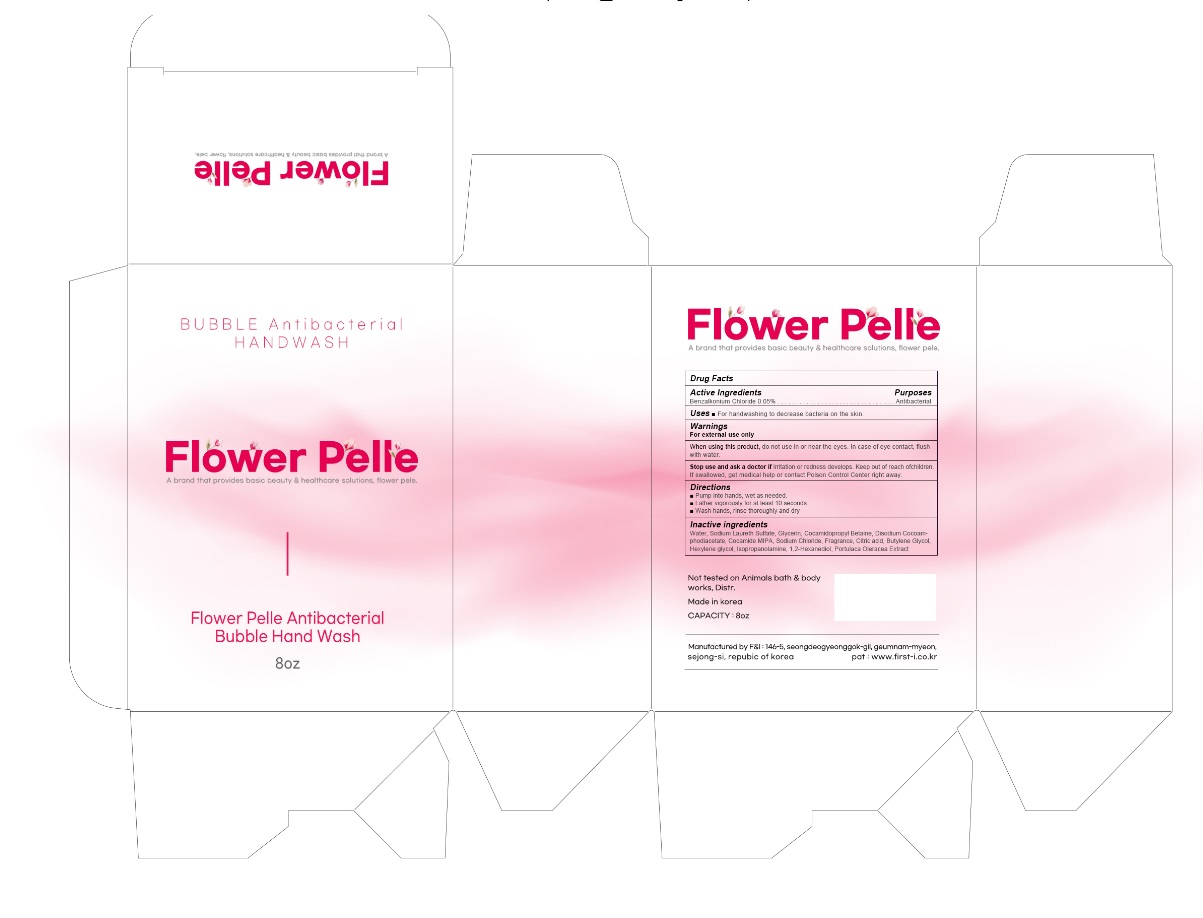 DRUG LABEL: Flower Pelle Bubble Antibacterial Hand Wash
NDC: 81328-001 | Form: LIQUID
Manufacturer: F&I
Category: otc | Type: HUMAN OTC DRUG LABEL
Date: 20201222

ACTIVE INGREDIENTS: BENZALKONIUM CHLORIDE 0.05 g/100 mL
INACTIVE INGREDIENTS: WATER; SODIUM LAURETH-3 SULFATE; GLYCERIN; COCAMIDOPROPYL BETAINE; DISODIUM COCOAMPHODIACETATE; COCO MONOISOPROPANOLAMIDE; SODIUM CHLORIDE; CITRIC ACID MONOHYDRATE; BUTYLENE GLYCOL; HEXYLENE GLYCOL; ISOPROPANOLAMINE; 1,2-HEXANEDIOL; PURSLANE

81328-001_Flower Pelle Bubble Antibacterial Hand Wash

Active ingredient

Benzalkonium Chloride 0.05%

Purpose

Antimicrobial

Use

- For hand sanitizer to decrease bacteria on the skin

Warnings

For external use only

When using this product, do not use in or near the eyes. In case of eye contact, flush with water.

Stop use and ask a doctor if irritation or rash appears and lasts

Keep out of reach of children, except under adult supervision. If swallowed, get medical help or contact a Poison Control Center right away

Directions

Pump into hands, wet as needed.
Lather vigorously for at least 10 seconds.
Wash hands, rinse thoroughly and dry

Inactive ingredients

Water, Sodium Laureth Sulfate, Glycerin, Cocamidopropyl Betaine, Disodium Cocoamphodiacetate, Cocamide MIPA, Sodium Chloride, Fragrance, Citric acid, Butylene Glycol, Hexylene glycol, Isopropanolamine, 1,2-Hexanediol, Portulaca Oleracea Extract